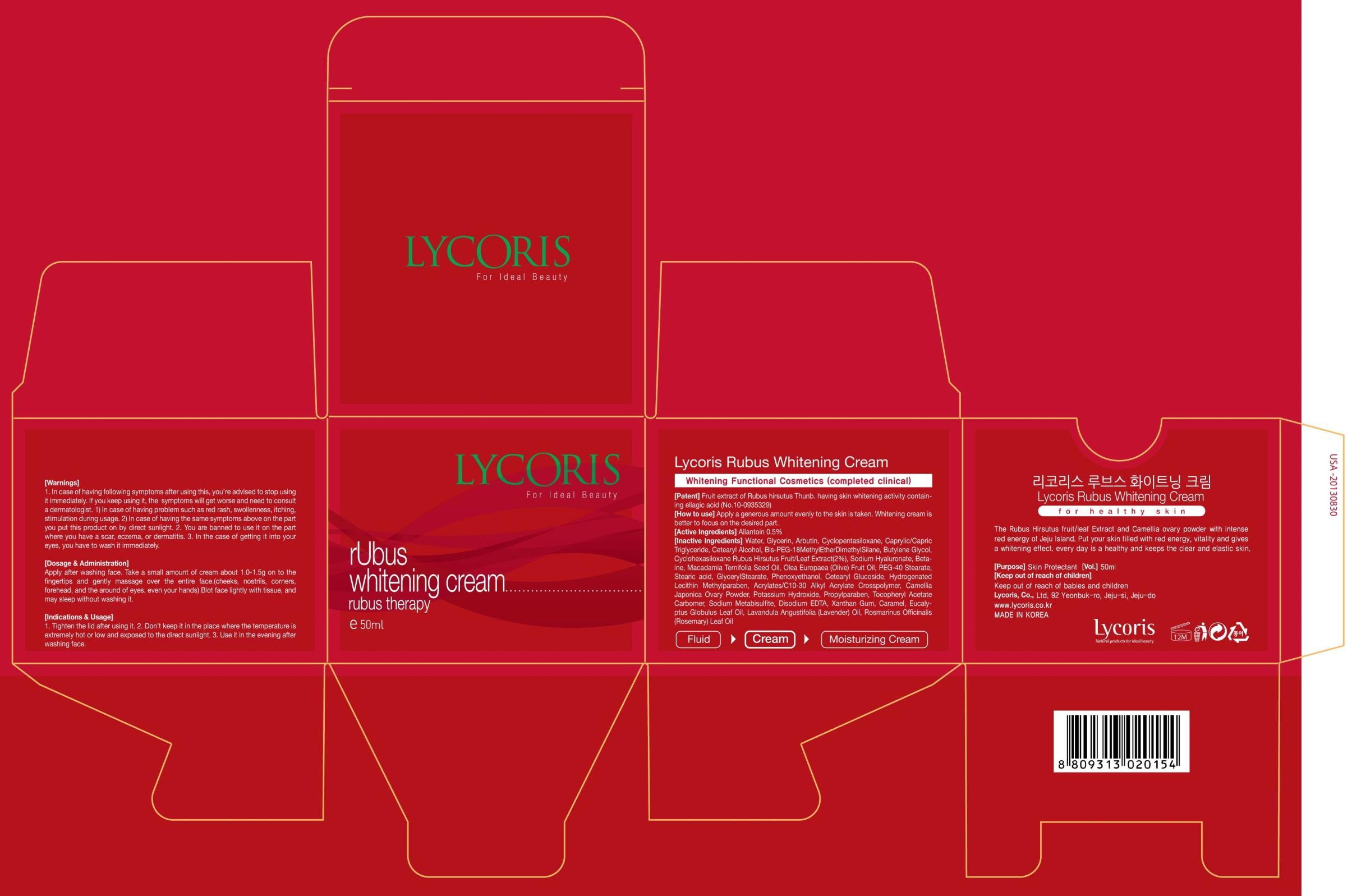 DRUG LABEL: Lycoris rubus whitening
NDC: 60778-030 | Form: CREAM
Manufacturer: Lycoris Co., Ltd.
Category: otc | Type: HUMAN OTC DRUG LABEL
Date: 20131008

ACTIVE INGREDIENTS: Allantoin 0.25 mg/50 mL
INACTIVE INGREDIENTS: Water; Glycerin

ACTIVE INGREDIENT

Active Ingredient: Allantoin 0.5%

INACTIVE INGREDIENT

Inactive Ingredients: Water, Glycerin, Arbutin, Cyclopentasiloxane, Caprylic/Capric Triglyceride, Cetearyl Alcohol, Bis-PEG-18MethylEtherDimethylSilane, Butylene Glycol, Cyclohexasiloxane Rubus Hirsutus Fruit/Leaf Extract(2%), Sodium Hyaluronate, Betaine,Macadamia Ternifolia Seed Oil, Olea Europaea (Olive) Fruit Oil, PEG-40 Stearate, Stearic acid, GlycerylStearate, Phenoxyethanol, Cetearyl Glucoside, Hydrogenated Lecithin Methylparaben, Acrylates/C10-30 Alkyl Acrylate Crosspolymer, Camellia Japonica Ovary Powder, Potassium Hydroxide, Propylparaben, Tocopheryl Acetate Carbomer, Sodium Metabisulfite, Disodium EDTA, Xanthan Gum, Caramel, Eucalyptus Globulus Leaf Oil, Lavandula Angustifolia (Lavender) Oil, Rosmarinus Officinalis (Rosemary) Leaf Oil

PURPOSE

Purpose: Skin Protectant

WARNINGS

Warnings: 1. In case of having following symptoms after using this, you're advised to stop using it immediately. If you keep using it, the symptoms will get worse and need to consult a dermatologist. 1) In case of having problem such as red rash, swollenness, itching, stimulation during usage. 2) In case of having the same symptoms above on the part you put this product on by direct sunlight. 2. You are banned to use it on the part where you have a scar, eczema, or dermatitis. 3. In the case of getting it into your eyes, you have to wash it immediately.

KEEP OUT OF REACH OF CHILDREN

Keep out of reach of babies and children

Indications and usage: 1. Tighten the lid after using it. 2. Don't keep it in the place where the temperature is extremely hot or low and exposed to the direct sunlight. 3. Use it in the evening after washing face.

Dosage and administration: Apply after washing face. Take a small amount of cream about 1.0-1.5g on to the fingertips and gently massage over the entire face.(cheeks, nostrils, corners, forehead, and the around of eyes, even your hands) Blot face lightly with tissue, and may sleep without washing it.